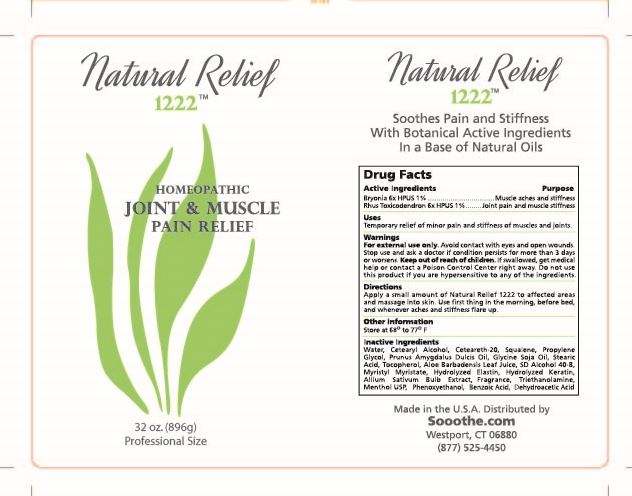 DRUG LABEL: Natural Relief 1222
NDC: 76348-480 | Form: LOTION
Manufacturer: RENU LABORATORIES, INC.
Category: homeopathic | Type: HUMAN OTC DRUG LABEL
Date: 20220117

ACTIVE INGREDIENTS: TOXICODENDRON PUBESCENS LEAF 2.24 g/224 g; BRYONIA ALBA ROOT 2.24 g/224 g
INACTIVE INGREDIENTS: STEARIC ACID; PHENOXYETHANOL; GARLIC; PROPYLENE GLYCOL; MYRISTYL MYRISTATE; SQUALANE; WHITE WAX; WATER; TROLAMINE; .ALPHA.-TOCOPHEROL; HYDROLYZED BOVINE ELASTIN (BASE; 1000 MW); MARINE COLLAGEN, SOLUBLE; MENTHOL; ALMOND OIL; SOYBEAN OIL; ALOE VERA LEAF; BENZOIC ACID; DEHYDROACETIC ACID

Natural Relief 1222

ACTIVE INGREDIENT

Bryonia 6x HPUS 1%

Rhus Toxicodendron 6x HPUS 1%

WARNINGS

For external use only Avoid contact with eyes and open wounds. Stop use and ask a doctor if condition persists for more than 3 days or worsens. Keep out of reach of children. If swallowed, get medical help or contact a Poison Control Center right away. Do not use this product if you are hypersensitive to any of the ingredients.

Stop use and ask a doctor if condition persists for more than 3 days or worsens.

Keep out of reach of children.

PURPOSE

Muscle aches and stiffness

Joint pain and muscle stiffness

INDICATIONS AND USAGE

Temporry relief of minor pain and stiffness of muscles and joints.

Directions

Apply a small amount of Natural Relief 1222 to affected areas and massage into skin. Use first thing in the morning, before bed, and whenever aches and stiffness flare up.

OTHER SAFETY INFORMATION

Store at 68 ° to 77° F.

STATEMENT OF IDENTITY

Natural Relief 1222 HOMEOPATHIC JOINT & MUSCLE PAIN RELIEF

INACTIVE INGREDIENT

Water, Cetearyl Alcohol, Ceteareth-20, Squalene, Propylene Glycol, Prunus Amygdalus Dulcis Oil, Glycine Soja Oil,

Stearic Acid, Tocopherol, Aloe Barbadensis Leaf Juice, SD Alcohol 40-B, Myristyl Myristate, Hydrolyzed Elastin, Hydrolyzed Keratin,

Allium Sativum Bulb Extract, Fragrance, Triethanolamine, Menthol USP, Phenoxyethanol, Benzoic Acid, Dehydroacetic Acid

NATURAL RELIEF 1222 LABEL FOR 32 OZ.